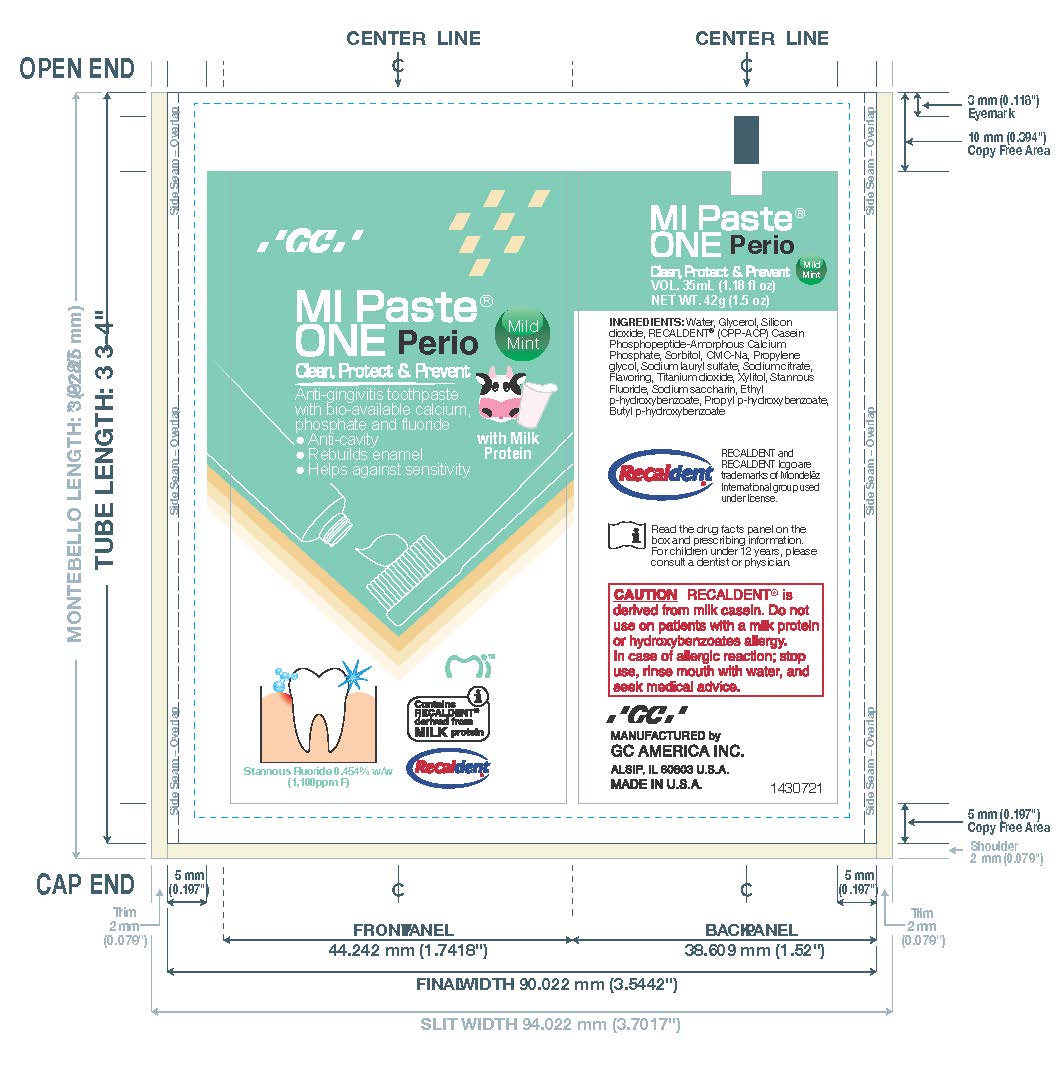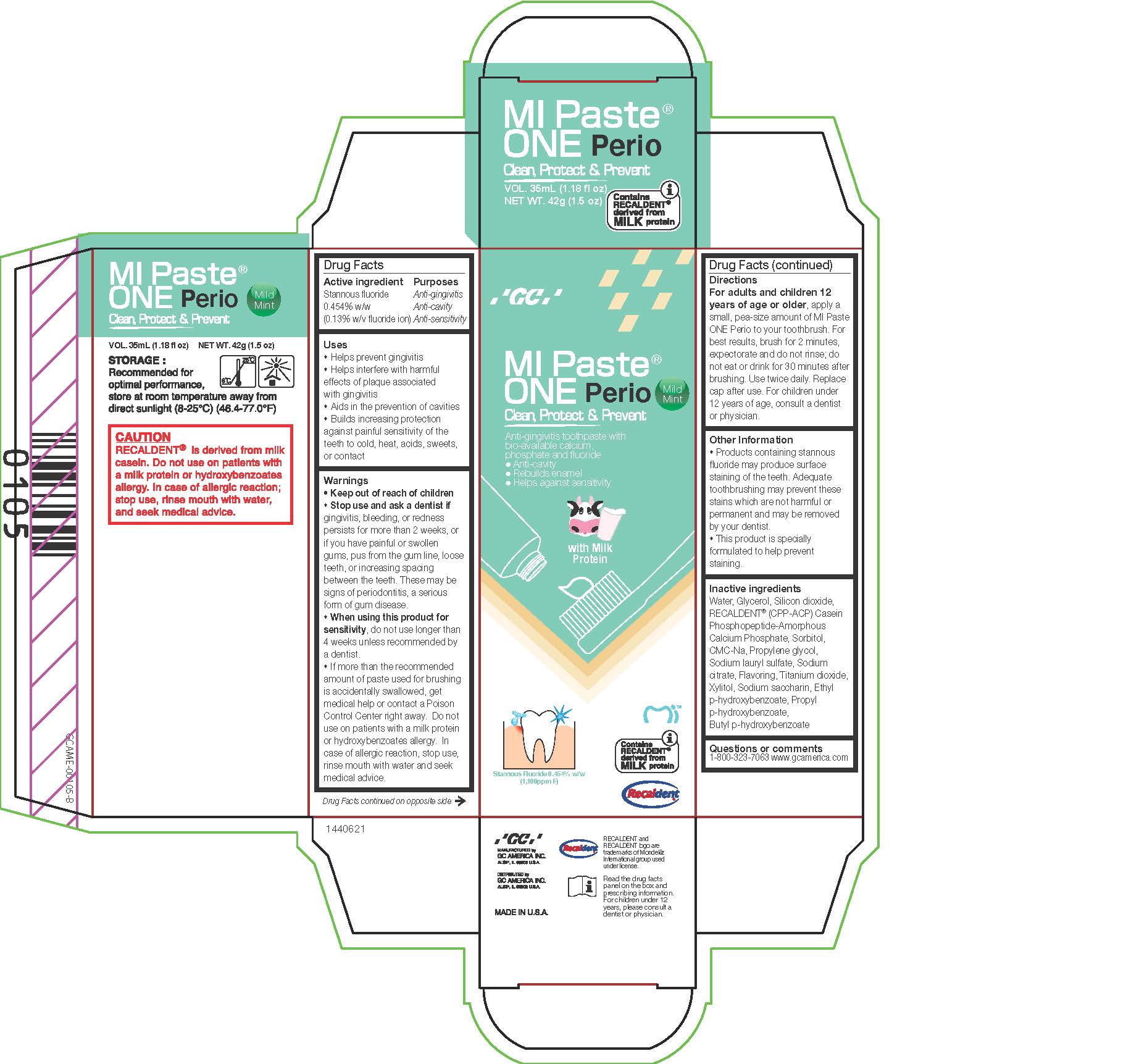 DRUG LABEL: MIPaste One Perio
NDC: 61596-300 | Form: PASTE, DENTIFRICE
Manufacturer: GC America Inc.
Category: otc | Type: HUMAN OTC DRUG LABEL
Date: 20251219

ACTIVE INGREDIENTS: STANNOUS FLUORIDE 0.454 g/100 g
INACTIVE INGREDIENTS: WATER; CALCIUM PHOSPHATE, UNSPECIFIED FORM; CARBOXYMETHYLCELLULOSE SODIUM, UNSPECIFIED; GLYCERIN; SILICON DIOXIDE; SACCHARIN SODIUM; ETHYLPARABEN; PROPYLENE GLYCOL; SORBITOL; SODIUM LAURYL SULFATE; XYLITOL; PROPYLPARABEN; BUTYLPARABEN; SODIUM CITRATE, UNSPECIFIED FORM; TITANIUM DIOXIDE

MIPaste One Perio

Active ingredient
Stannous fluoride
0.454% w/w
(0.13% w/v fluoride ion)

Inactive ingredients
Water, Glycerol, Silicon dioxide,
RECALDENT® (CPP-ACP) Casein
Phosphopeptide-Amorphous
Calcium Phosphate, Sorbitol,
CMC-Na, Propylene glycol,
Sodium lauryl sulfate, Sodium
citrate, Flavoring, Titanium dioxide,
Xylitol, Sodium saccharin, Ethyl
p-hydroxybenzoate, Propyl
p-hydroxybenzoate,
Butyl p-hydroxybenzoate

• Keep out of reach of children
• Stop use and ask a dentist if
gingivitis, bleeding, or redness
persists for more than 2 weeks, or
if you have painful or swollen
gums, pus from the gum line, loose
teeth, or increasing spacing
between the teeth. These may be
signs of periodontitis, a serious
form of gum disease.
• When using this product for
sensitivity, do not use longer than
4 weeks unless recommended by
a dentist.
• If more than the recommended
amount of paste used for brushing
is accidentally swallowed, get
medical help or contact a Poison
Control Center right away. Do not
use on patients with a milk protein
or hydroxybenzoates allergy. In
case of allergic reaction, stop use,
rinse mouth with water and seek
medical advice.

DOSAGE AND ADMINISTRATION

For adults and children 12
years of age or older, apply a
small, pea-size amount of MI Paste
ONE Perio to your toothbrush. For
best results, brush for 2 minutes,
expectorate and do not rinse; do
not eat or drink for 30 minutes after
brushing. Use twice daily. Replace
cap after use. For children under
12 years of age, consult a dentist
or physician.

Uses
• Helps prevent gingivitis
• Helps interfere with harmful
effects of plaque associated
with gingivitis
• Aids in the prevention of cavities
• Builds increasing protection
against painful sensitivity of the
teeth to cold, heat, acids, sweets,
or contact

• Keep out of reach of children

Purposes
Anti-gingivitis
Anti-cavity
Anti-sensitivity